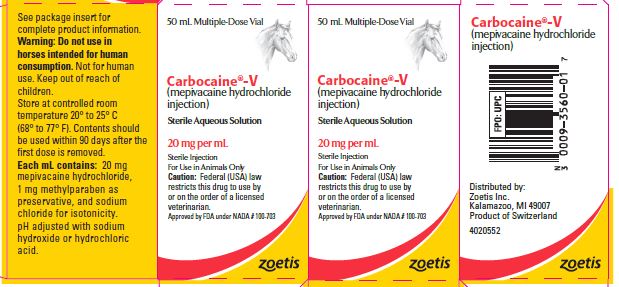 DRUG LABEL: Carbocaine
NDC: 54771-3560 | Form: SOLUTION
Manufacturer: Zoetis Inc.
Category: animal | Type: PRESCRIPTION ANIMAL DRUG LABEL
Date: 20240606

ACTIVE INGREDIENTS: MEPIVACAINE HYDROCHLORIDE 20 mg/1 mL
INACTIVE INGREDIENTS: METHYLPARABEN 1 mg/1 mL; SODIUM CHLORIDE; SODIUM HYDROXIDE; HYDROCHLORIC ACID

Carbocaine®-V
(mepivacaine hydrochloride injection)
Sterile Aqueous Solution

Local Anesthetic with Rapid and Prolonged Effect for Use in Horses

Caution

Federal (USA) law restricts this drug to use by or on the order of a licensed veterinarian.

DESCRIPTION

Mepivacaine hydrochloride, 1-methyl-2', 6'-pipecoloxylidide monohydrochloride, is a white, crystalline, odorless powder, readily soluble in water, and very stable in aqueous solution. It is available as a 2% sterile aqueous solution containing sodium chloride (for isotonicity) and 0.1% methylparaben (as preservative). The pH is adjusted with sodium hydroxide or hydrochloric acid.

CLINICAL PHARMACOLOGY

Mepivacaine hydrochloride is a potent local anesthetic whose effectiveness and safety have been well established in human medicine and dentistry. Laboratory and clinical studies in animals have confirmed its value in veterinary medicine. Its anesthetic activity is two to two and one half times that of procaine, and it is equal to or better than that of lidocaine. The compound has shown excellent tissue compatibility in laboratory animals and in horses. Moderate transient edema at the site of injection may occur in rare instances.

CARBOCAINE-V Sterile Aqueous Solution produces rapid and marked local anesthesia lasting for several hours. This enables the veterinarian to proceed with intended manipulations without delay and to complete the work under desensitization which is adequate even for prolonged operations. The innate vasoconstrictive activity of CARBOCAINE-V Sterile Aqueous Solution may be enhanced by the addition of epinephrine at 1:100,000. The addition should be carried out aseptically for current use and any unused portion should be discarded.

INDICATIONS

CARBOCAINE-V Sterile Aqueous Solution is recommended for infiltration, nerve block, intra-articular and epidural anesthesia for horses. It has also been found useful for topical anesthesia of the laryngeal mucosa prior to ventriculectomy. As with other anesthetics, the dosage varies considerably depending on the anesthetic technique, body area to be desensitized and the surgical procedure.

WARNINGS

Do not use in horses intended for human consumption. Not for human use. Keep out of reach of children.

PRECAUTIONS

When administered by a skilled person, CARBOCAINE-V Sterile Aqueous Solution may be employed safely for local infiltration, for common nerve blocking procedures, and for intra-articular and epidural anesthesia.

The following precautions, which are observed with respect to all local anesthetics, also apply to this anesthetic. (1) Injections should always be made aseptically and with frequent aspirations. If blood is aspirated, the needle should be relocated and the injections continued cautiously. (2) When used for epidural anesthesia, care should be taken to avoid injection into the subarachnoid space. The skin should be shaved and sterilized, and the needles used must be sharp and of the proper length. (3) The depth of anesthesia should be checked by pricking the area before manipulations are begun.

DOSAGE AND ADMINISTRATION

Pharmacological studies in various species of animals, including horses, have shown that the drug produces complete and effective anesthesia at dosages that are no more than half those needed when procaine is used.

The following dosages have generally proved satisfactory in the horse and are therefore suggested as a guide:

For nerve block
(diagnosis of lameness, firing, pain relief in osteoarthritis, navicular disease)— 3 to 15 mL

For epidural anesthesia
(animal standing)— 5 to 20 mL

For intra-articular anesthesia
(removal of fracture chips, bone and bog spavin, arthritis)— 10 to 15 mL

For infiltration
(alone or in combination with nerve block or intra-articular anesthesia)— as required

For anesthesia of the laryngeal mucosa prior to ventriculectomy CARBOCAINE-V Sterile Aqueous Solution may be administered topically or by infiltration or by a combination of the two. For topical application, a total of 25 to 40 mL applied by spray (3 mL/application) is usually adequate. For infiltration, 20 to 50 mL will suffice.

HOW SUPPLIED

CARBOCAINE-V is available as 50 mL Multiple-Dose Vials.

Each mL contains 20 mg mepivacaine hydrochloride, 1 mg methylparaben as preservative, and sodium chloride for isotonicity. The pH was adjusted with sodium hydroxide or hydrochloric acid.

Store at controlled room temperature 20° to 25° C (68° to 77° F). Contents should be used within 90 days after the first dose is removed.

Approved by FDA under NADA # 100-703

Distributed by:
Zoetis Inc
Kalamazoo, MI 49007

Revised: August 2019

4020551 - PH 1085